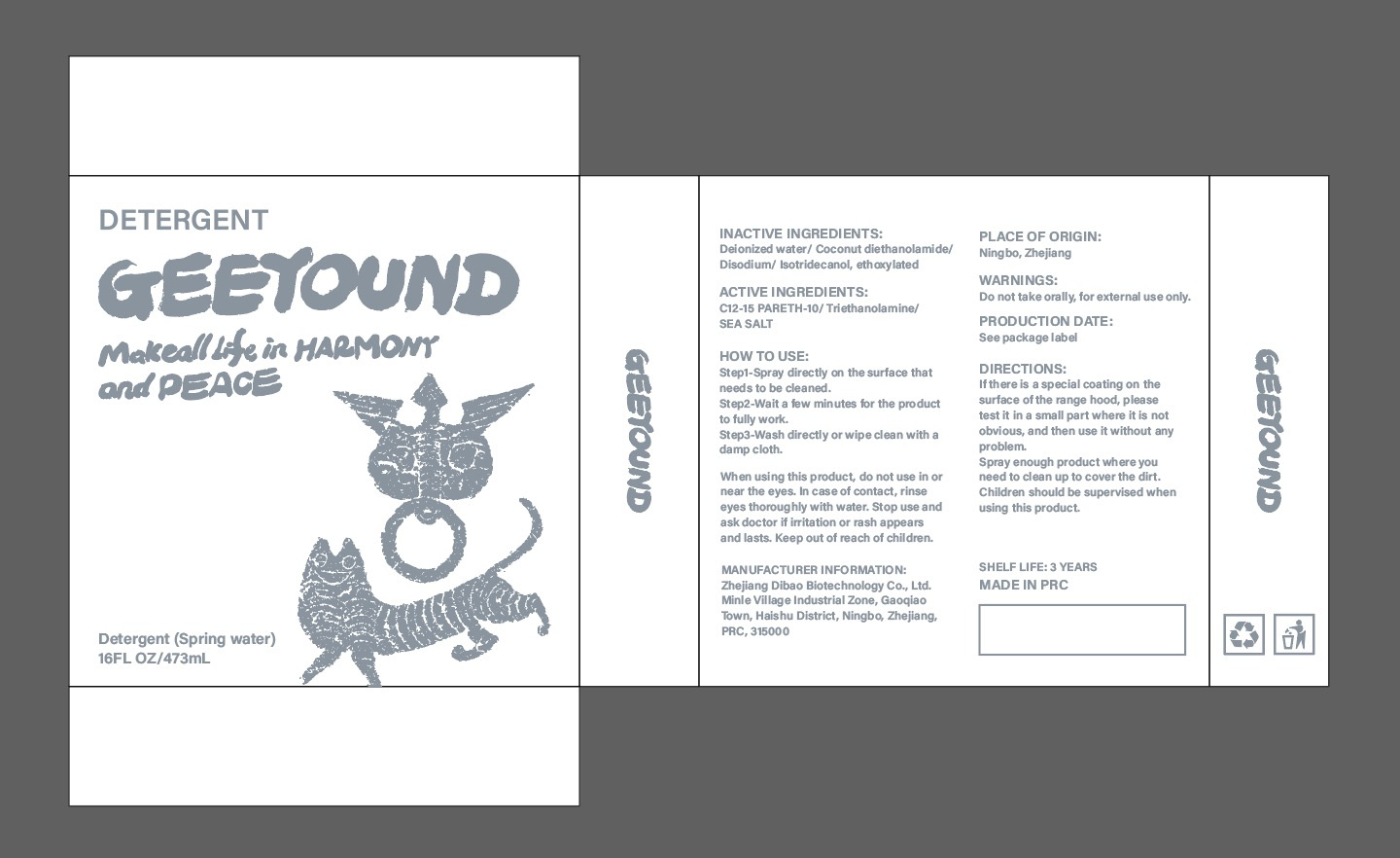 DRUG LABEL: Detergent
NDC: 82371-009 | Form: LIQUID
Manufacturer: Zhejiang Dibao Biotechnology Co., Ltd.
Category: otc | Type: HUMAN OTC DRUG LABEL
Date: 20220104

ACTIVE INGREDIENTS: TROLAMINE 4 g/100 mL; SEA SALT 10.2 g/100 mL; C12-15 PARETH-10 5 g/100 mL
INACTIVE INGREDIENTS: WATER; COCO DIETHANOLAMIDE; SODIUM PHOSPHATE, DIBASIC, DIHYDRATE

ACTIVE INGREDIENT

C12-15 PARETH-10 5%

Triethanolamine 4%

SEA SALT 10.2%

INACTIVE INGREDIENT

Deionized water

Coconut diethanolamide

Disodium

Isotridecanol, ethoxylated

HOW TO USE

Step1-Spray directly on the surface that needs to be cleaned.
Step2-Wait a few minutes for the product to fully work.
Step3-Wash directly or wipe clean with a damp cloth.
When using this product, do not use in or near the eyes. ln case of contact, rinse eyes thoroughly with water.Stop use and ask doctor if irritation or rash appears and lasts. Keep out of reach of children.

DIRECTIONS

lf there is a special coating on the surface of the range hood, please test it in a small part where it is not obvious,and then use it without any problem.
Spray enough product where you need to clean up to cover the dirt.Children should be supervised when using this product.

Keep out of reach of children.

PURPOSE

clean

STORAGE AND HANDLING

Keep in a cool and dry place

WARNINGS

Do not take orally, for external use only